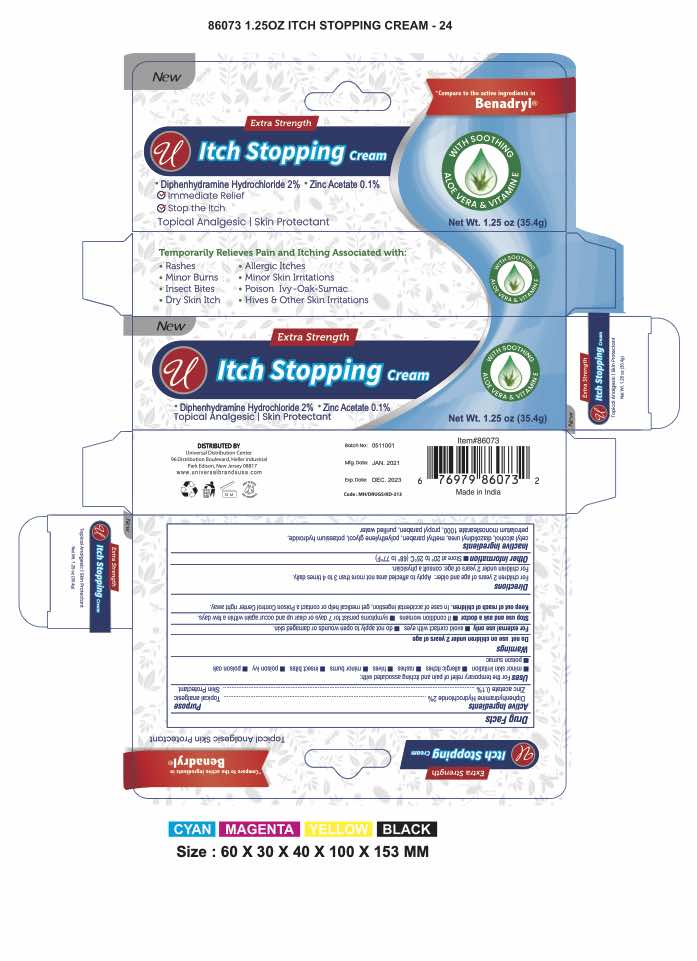 DRUG LABEL: Extra Strength
NDC: 52000-071 | Form: CREAM
Manufacturer: Universal Distribution Centre LLC
Category: otc | Type: HUMAN OTC DRUG LABEL
Date: 20240513

ACTIVE INGREDIENTS: DIPHENHYDRAMINE HYDROCHLORIDE 20 mg/1 g; ZINC ACETATE 1 mg/1 g
INACTIVE INGREDIENTS: PROPYLPARABEN; WATER; POTASSIUM HYDROXIDE; CETYL ALCOHOL; DIAZOLIDINYL UREA; METHYLPARABEN; PROPYLENE GLYCOL

EXTRA STRENGTH ITCH STOPPING CREAM

Uses

- temporarily relieves pain and itching associated with:
  - insect bites
  - minor burns
  - sunburn
  - minor skin irritations
  - minor cuts
  - scrapes
  - rashes due to poison ivy, poison oak, and poison sumac
- dries the oozing and weeping of poison ivy, poison oak, and poison sumac

Drug Facts

ACTIVE INGREDIENT

Active ingredients | Purpose
Diphenhydramine hydrochloride 2% | Topical analgesic
Zinc acetate 0.1% | Skin protectant

Warnings

For external use only

Do not use

- on large areas of the body
- with any other product containing diphenhydramine, even one taken by mouth

Ask a doctor before use

- on chicken pox
- on measles

When using this product avoid contact with eyes

Stop use and ask a doctor if

- condition worsens or does not improve within 7 days
- symptoms persist for more than 7 days or clear up and occur again within a few days

Keep out of reach of children. If swallowed, get medical help or contact a Poison Control Center right away.

Directions

- do not use more than directed
- adults and children 2 years of age and older: apply to affected area not more than 3 to 4 times daily
- children under 2 years of age: ask a doctor

Other information

- protect from excessive heat (40°C/104°F)

Inactive ingredients

cetyl alcohol, diazolidinyl urea, methylparaben, polyethylene glycol monostearate 1000, propylene glycol, propylparaben, purified water

Questions?

Call toll-free 1-800-222-1222

Distributed by:
Universal Distribution Centre LLC

96 Distribution Boulevard, Edison
NJ 08817

PRINCIPAL DISPLAY PANEL - 35.4 g Tube Carton

EXTRA STRENGTH

Topical Analgesic/Skin Protectant

ITCH
STOPPING
CREAM

NET WT 1.25 OZ (35.4 g)